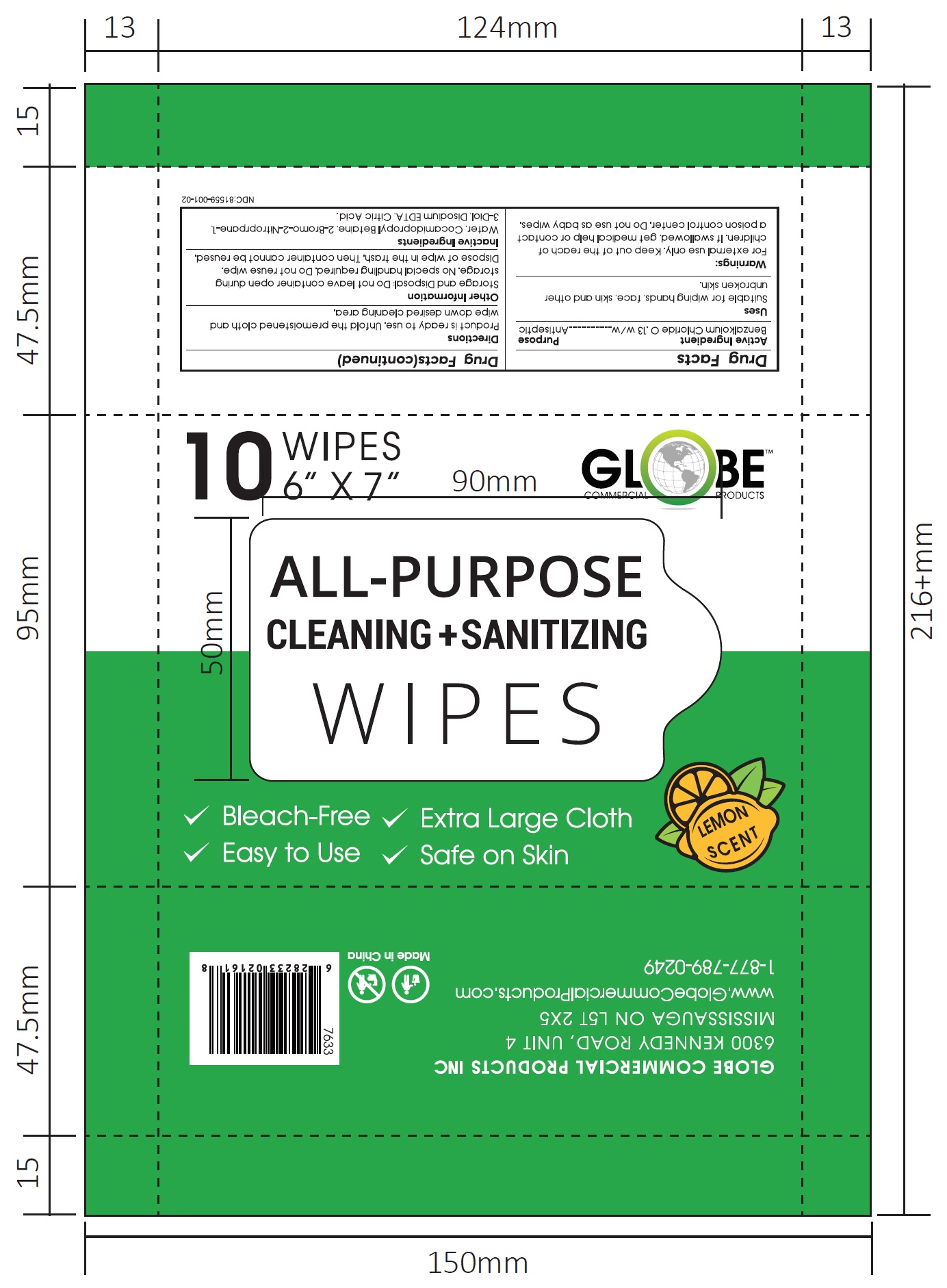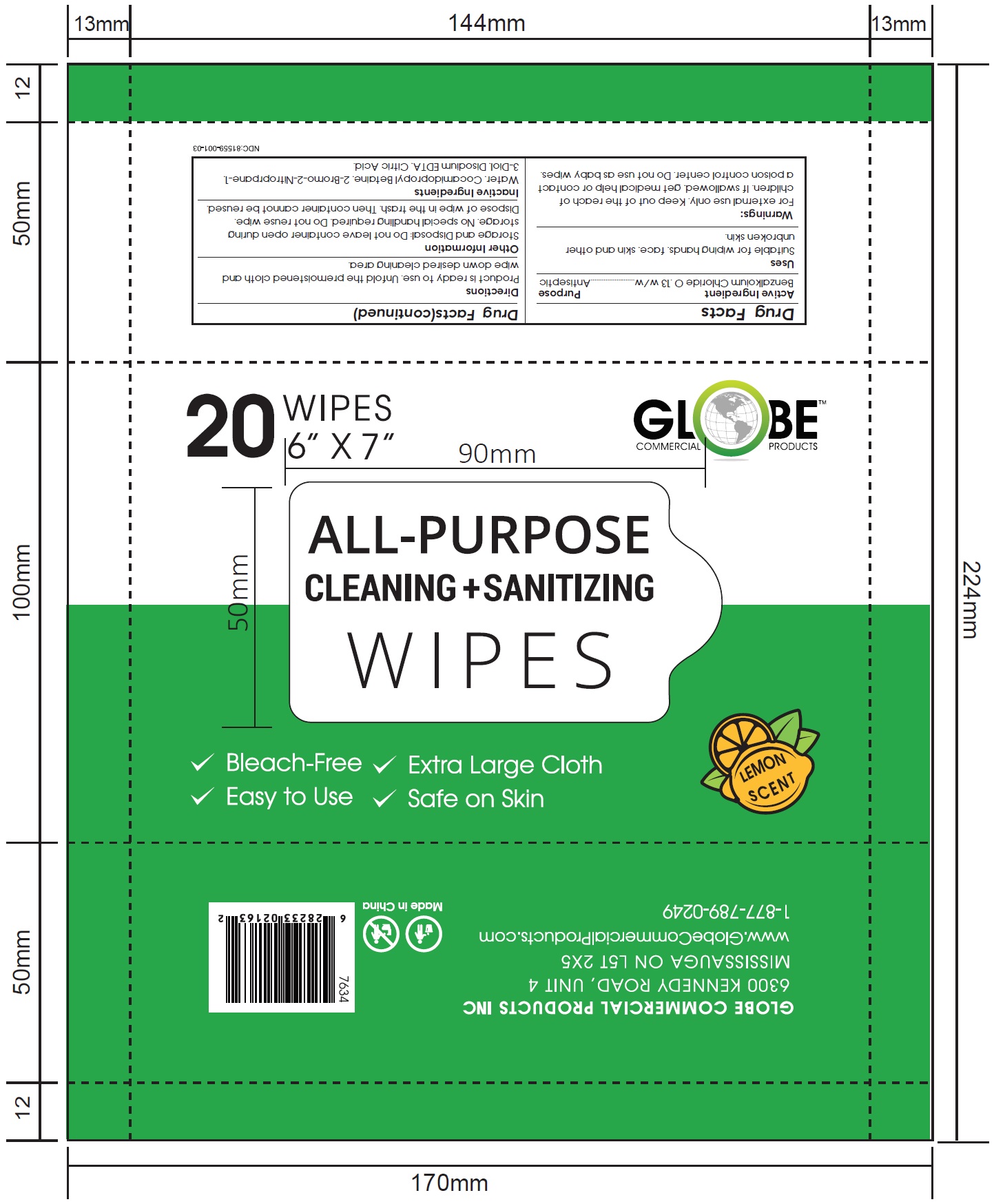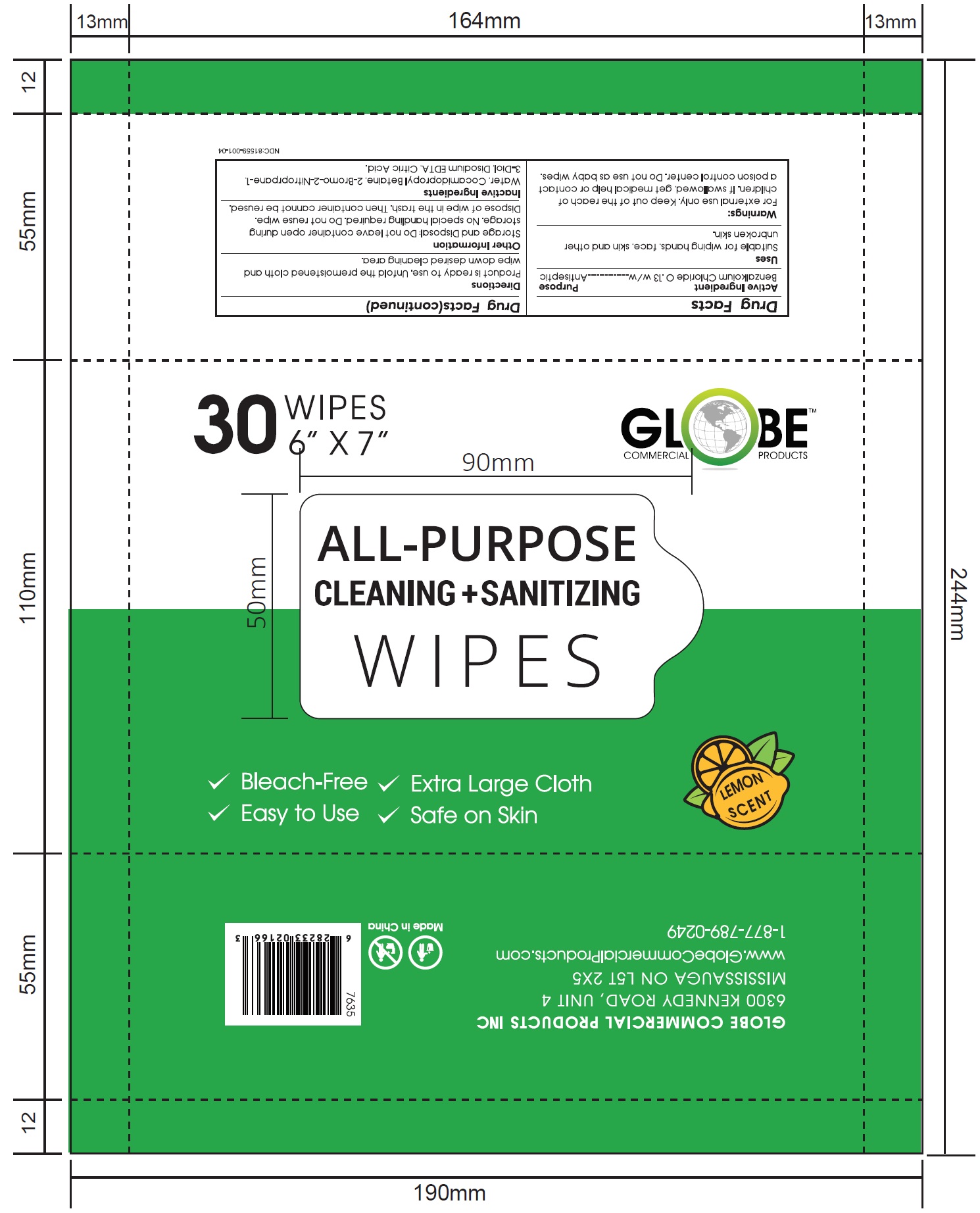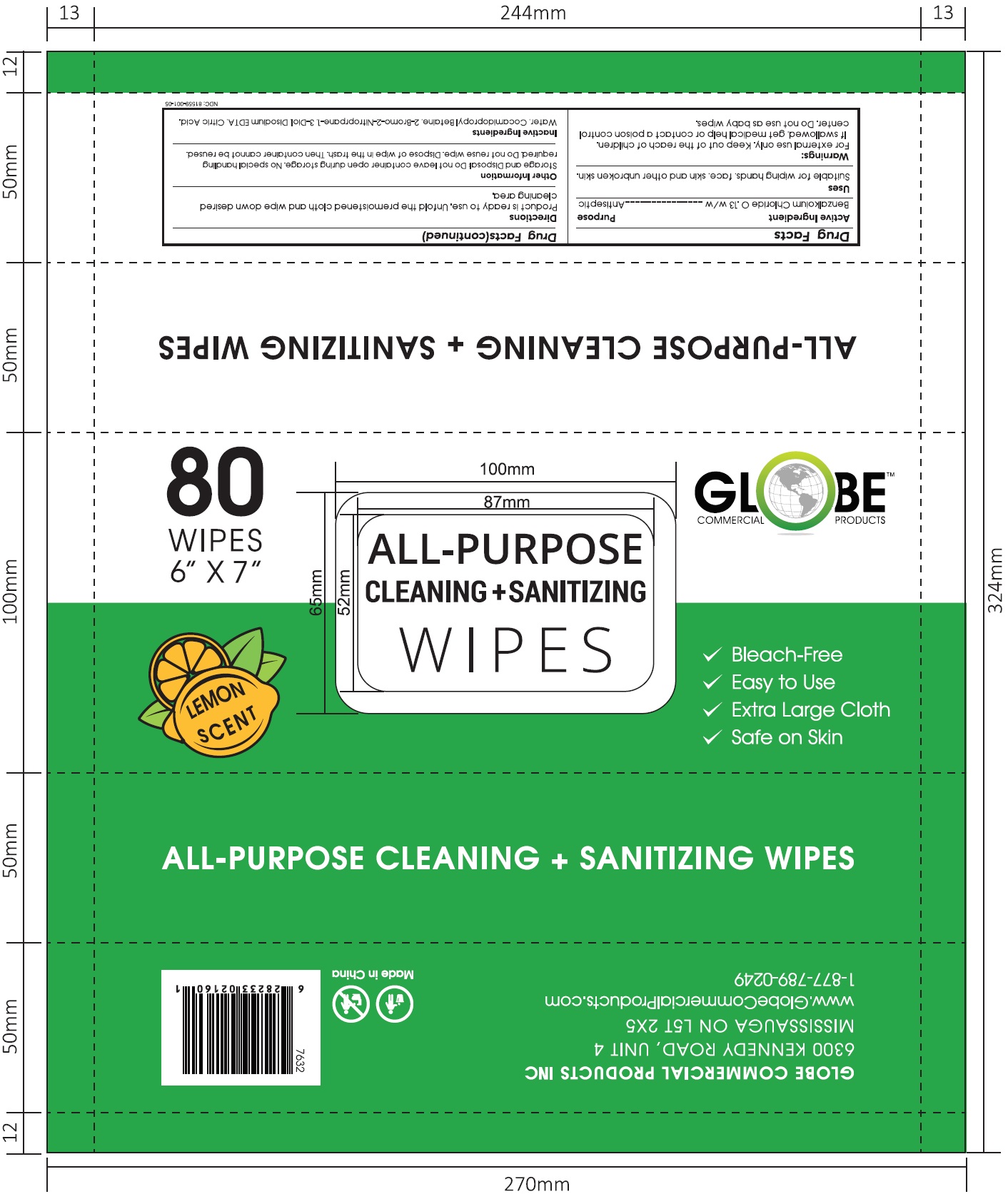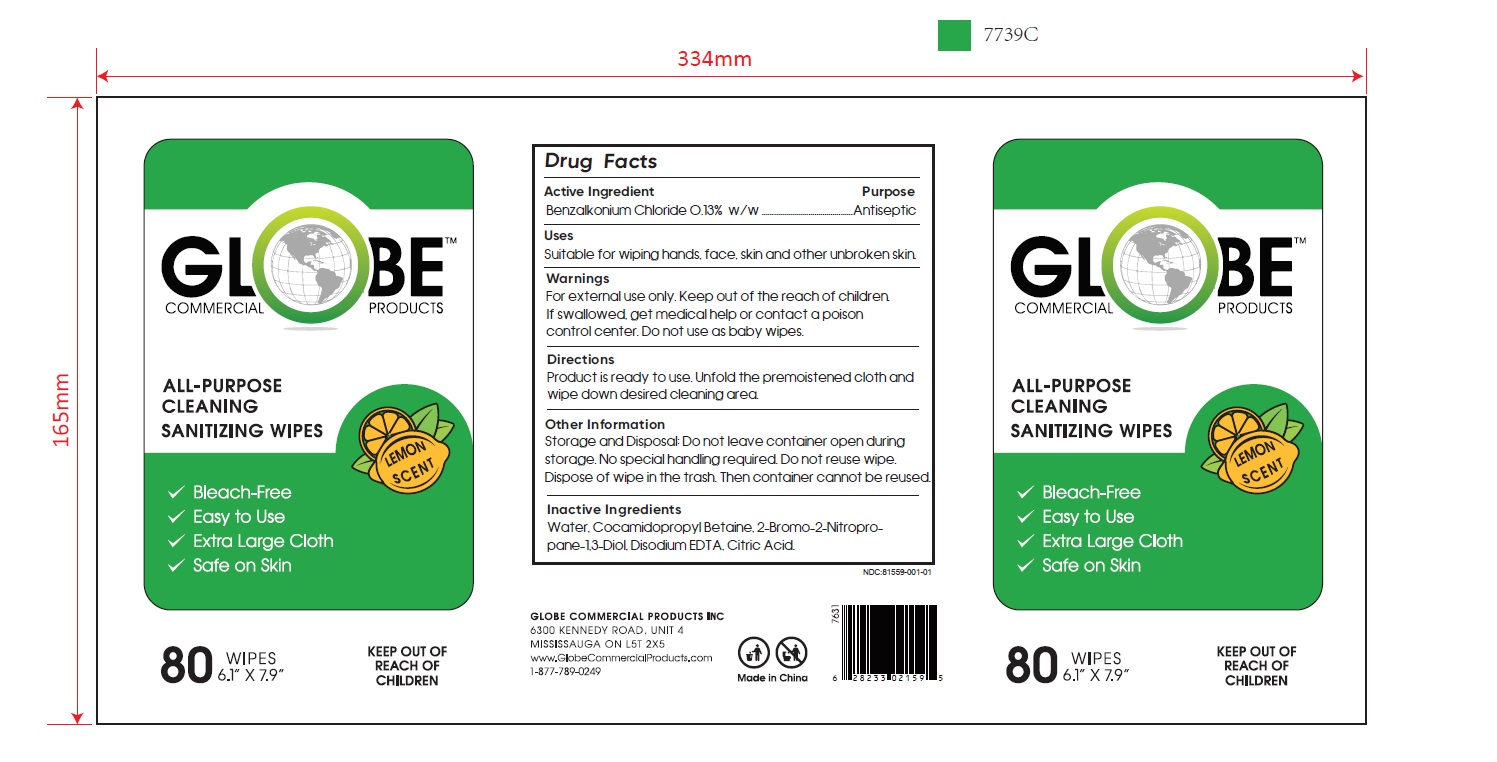 DRUG LABEL: All Purpose Cleaning and Sanitizing Wipes
NDC: 81559-001 | Form: CLOTH
Manufacturer: Globe Commercial Products Inc
Category: otc | Type: HUMAN OTC DRUG LABEL
Date: 20210629

ACTIVE INGREDIENTS: BENZALKONIUM CHLORIDE 0.13 g/100 g
INACTIVE INGREDIENTS: WATER; COCO/OLEAMIDOPROPYL BETAINE; BRONOPOL; EDETATE CALCIUM DISODIUM ANHYDROUS; ANHYDROUS CITRIC ACID

All Purpose Cleaning and Sanitizing Wipes

Active Ingredient

Benzalkonium Chloride 0.13% w/w

Purpose

Antiseptic

Uses

Suitable for wiping hands, face, skin and other unbroken skin.

Warnings

For external use only. Keep out of the reach of children. If swallowed, get medical help or contact a poison control center. Do not use as baby wipes.

Keep out of the reach of children.

Directions

Product is ready to use. Unfold the premoistened cloth and wipe down desired cleaning area.

Other Information

Storage and Disposal: Do not leave container open during storage. No special handling required. Do not reuse wipe. Dispose of wipe in the trash. Then container cannot be reused.

Inactive Ingredients

Water, Cocamidopropyl Betaine, 2-Bromo-2-Nitropropane-1,3-Diol, Disodium EDTA, Citric Acid

PACKAGE LABEL

80 Wipes in a bottle, NDC: 81559-001-01

PACKAGE LABEL

10 Wipes, NDC: 81559-001-02

PACKAGE LABEL

20 Wipes, NDC: 81559-001-03

PACKAGE LABEL

30 Wipes, NDC: 81559-001-04

PACKAGE LABEL

80 Wipes, NDC: 81559-001-05